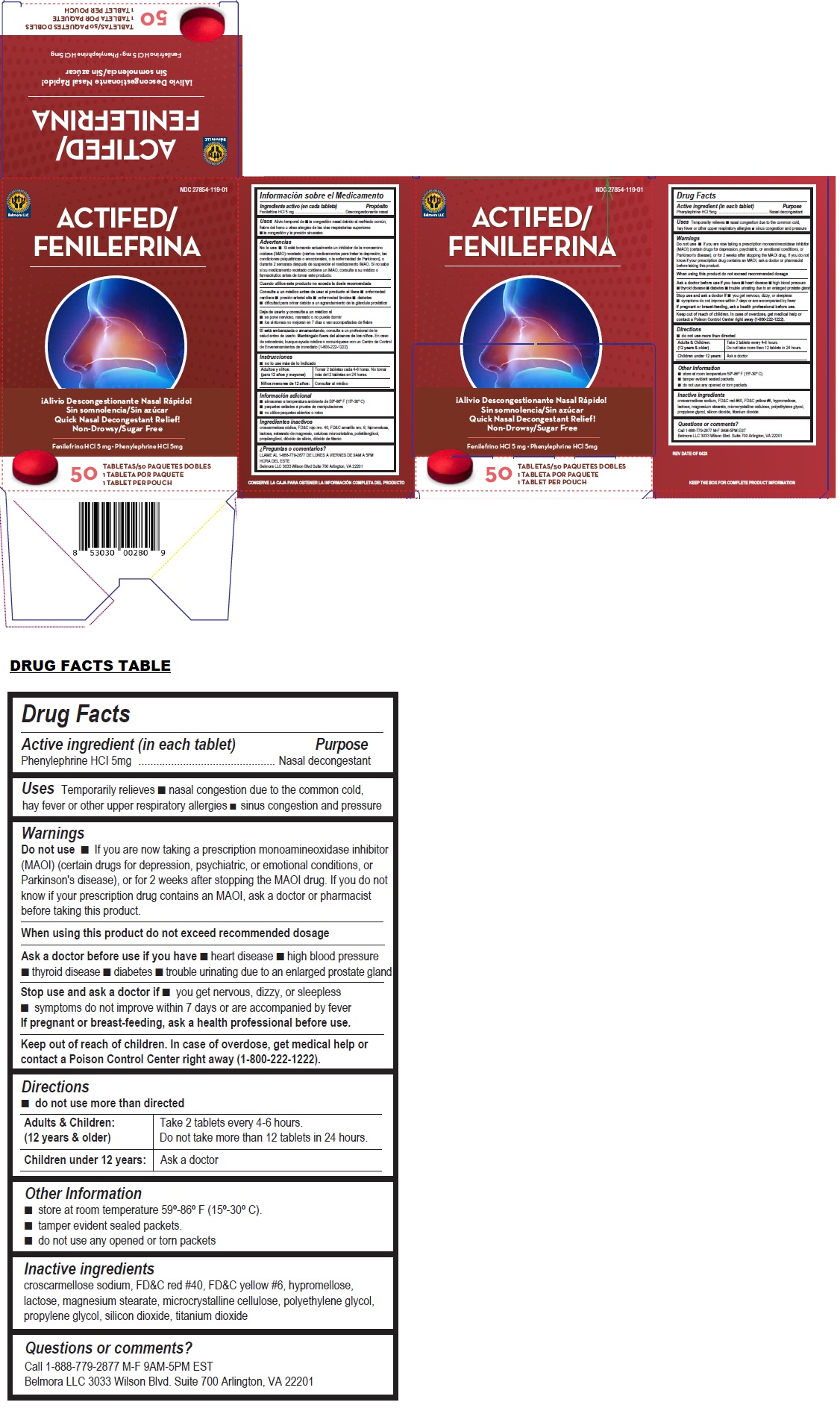 DRUG LABEL: ACTIFED
NDC: 27854-119 | Form: TABLET
Manufacturer: Belmora LLC
Category: otc | Type: HUMAN OTC DRUG LABEL
Date: 20241004

ACTIVE INGREDIENTS: PHENYLEPHRINE HYDROCHLORIDE 5 mg/1 1
INACTIVE INGREDIENTS: CROSCARMELLOSE SODIUM; FD&C RED NO. 40; FD&C YELLOW NO. 6; HYPROMELLOSE, UNSPECIFIED; LACTOSE, UNSPECIFIED FORM; MAGNESIUM STEARATE; MICROCRYSTALLINE CELLULOSE; POLYETHYLENE GLYCOL, UNSPECIFIED; PROPYLENE GLYCOL; SILICON DIOXIDE; TITANIUM DIOXIDE

ACTIFED

Active ingredient (in each tablet)

Phenylephrine HCl 5mg

Purpose

Nasal decongestant

Uses

Temporarily relieves • nasal congestion due to the common cold, hay fever or other upper respiratory allergies • sinus congestion and pressure

Warnings

Do not use • If you are now taking a prescription monoamineoxidase inhibitor (MAOI) (certain drugs for depression, psychiatric, or emotional conditions, or Parkinson's disease), or for 2 weeks after stopping the MAOI drug. If you do not know if your prescription drug contains an MAOI, ask a doctor or pharmacist before taking this product.

When using this product do not exceed recommended dosage

Ask a doctor before use if you have • heart disease • high blood pressure • thyroid disease • diabetes • trouble urinating due to an enlarged prostate gland

Stop use and ask a doctor if • you get nervous, dizzy, or sleepless • symptoms do not improve within 7 days or are accompanied by fever
If pregnant or breast-feeding, ask a health professional before use.

Keep out of reach of children. In case of overdose, get medical help or contact a Poison Control Center right away (1-800-222-1222).

Directions

• do not use more than directed

Adults & Children: (12 years & older) | Take 2 tablets every 4-6 hours. Do not take more than 12 tablets in 24 hours.
Children under 12 years: | Ask a doctor

Other Information

• store at room temperature 59°-86° F (15°-30° C).
• tamper evident sealed packets.
• do not use any opened or torn packets

Inactive ingredients

croscarmellose sodium, FD&C red #40, FD&C yellow #6, hypromellose, lactose, magnesium stearate, microcrystalline cellulose, polyethylene glycol, propylene glycol, silicon dioxide, titanium dioxide

Questions or comments?

Call 1-888-779-2877 M-F 9AM-5PM EST
Belmora LLC 3033 Wilson Blvd. Suite 700 Arlington, VA 22201

Quick Nasal Decongestant Relief!
Non-Drowsy/Sugar Free

KEEP THE BOX FOR COMPLETE PRODUCT INFORMATION